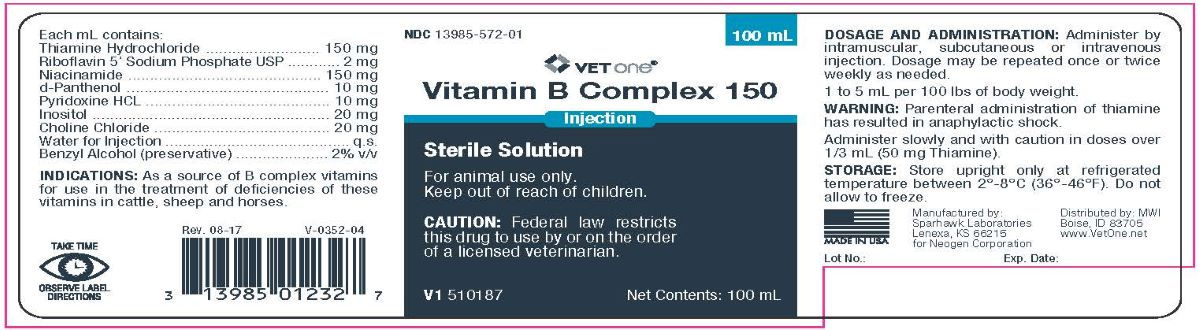 DRUG LABEL: Vitamin B Complex 150
NDC: 13985-572 | Form: INJECTION
Manufacturer: MWI/Vet One
Category: animal | Type: PRESCRIPTION ANIMAL DRUG LABEL
Date: 20231221

ACTIVE INGREDIENTS: THIAMINE HYDROCHLORIDE 150 mg/1 mL; RIBOFLAVIN 5'-PHOSPHATE SODIUM 2 mg/1 mL; NIACINAMIDE 150 mg/1 mL; PANTHENOL 10 mg/1 mL; PYRIDOXINE HYDROCHLORIDE 10 mg/1 mL; INOSITOL 20 mg/1 mL; CHOLINE CHLORIDE 20 mg/1 mL
INACTIVE INGREDIENTS: BENZYL ALCOHOL .02 mL/1 mL; WATER

Vitamin B Complex 150
Sterile Solution

Indications:

As a source of B complex vitamins for use in the treatment of deficiencies of these vitamins in cattle, sheep and horses.

Each mL Contains:

Thiamine Hydrochloride..................................................150 mg

Riboflavin 5' Sodium Phosphate USP....................................2 mg

Niacinamide..................................................................150 mg

d-Panthenol....................................................................10 mg

Pyridoxine HCL................................................................10 mg

Inositol..........................................................................20 mg

Choline Chloride..............................................................20 mg

Water for Injection...............................................................q.s.

Benzyl Alcohol (preservative)...........................................2% v/v

DOSAGE AND ADMINISTRATION:

Administer by intramuscular, subcutaneous or intravenous injection. Dosage may be repeated once or twice weekly as needed.

WARNING:

Parenteral administration of thiamine has resulted in anaphylactic shock.

Administer slowly and with caution in doses
over 1/3 mL (50 mg Thiamine).

STORAGE:

Store upright only at refrigerated temperature between 2º-8ºC (36º-46ºF). Do not allow to freeze.

Manufactured by:

Sparhawk Laboratories

Lenexa, KS 66215

for Neogen® Corporation

Distributed by: MWI

Boise, ID 83705

www.VetOne.net